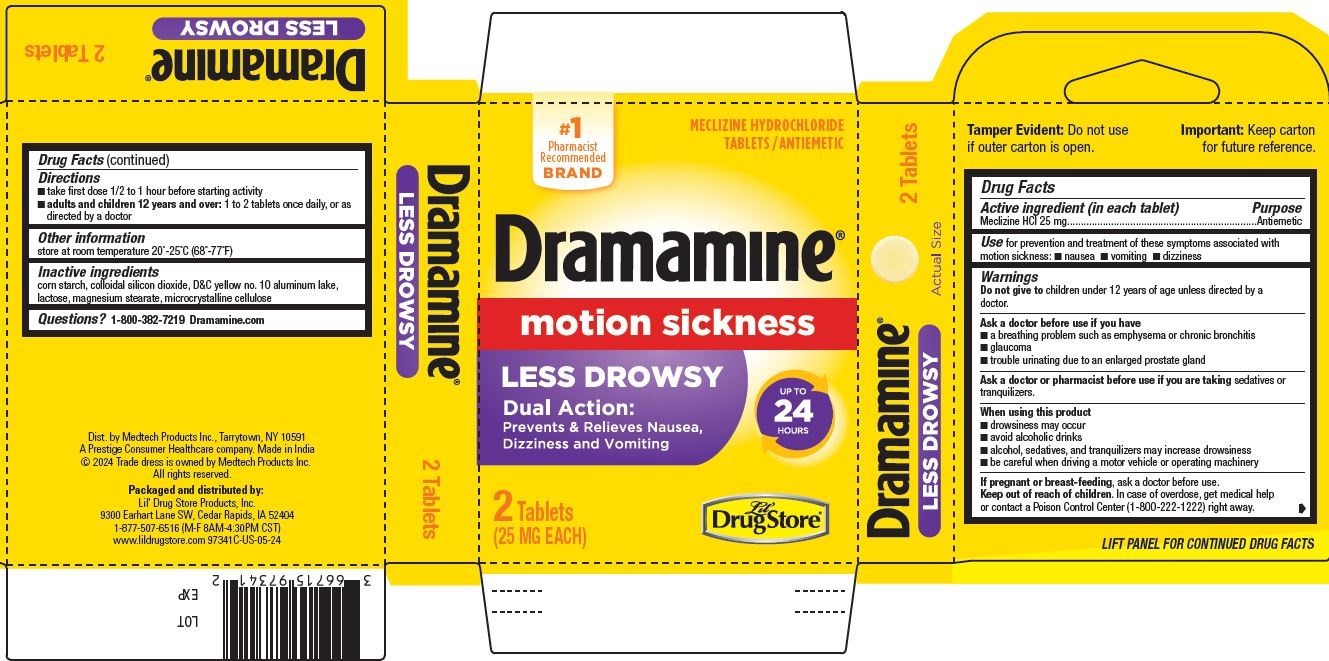 DRUG LABEL: Dramamine Less Drowsy, Lil Drug Store
NDC: 66715-9734 | Form: TABLET
Manufacturer: Lil' Drug Store Products, Inc.
Category: otc | Type: HUMAN OTC DRUG LABEL
Date: 20241120

ACTIVE INGREDIENTS: MECLIZINE HYDROCHLORIDE 25 mg/1 1
INACTIVE INGREDIENTS: D&C YELLOW NO. 10 ALUMINUM LAKE; LACTOSE, UNSPECIFIED FORM; CELLULOSE, MICROCRYSTALLINE; SILICON DIOXIDE; STARCH, CORN; MAGNESIUM STEARATE

Dramamine® Less Drowsy, Lil' Drug Store®

Active ingredient

Active ingredient (in each tablet)

Meclizine HCl 25 mg

Purpose

Antiemetic

Use

Use for prevention and treatment of these symptoms associated with
motion sickness:

- nausea
- vomiting
- dizziness

Warnings

Do not give to children under 12 years of age unless directed by a doctor.

Ask a doctor before use if you have

- a breathing problem such as emphysema or chronic bronchitis
- glaucoma
- trouble urinating due to an enlarged prostate gland

Ask a doctor or pharmacist before use if you are taking sedatives or tranquilizers.

When using this product

- drowsiness may occur
- avoid alcoholic drinks
- alcohol, sedatives, and tranquilizers may increase drowsiness
- be careful when driving a motor vehicle or operating machinery

If pregnant or breast-feeding, ask a doctor before use.

Keep out of reach of children. In case of overdose, get medical help or contact a Poison Control Center (1-800-222-1222) right away.

Directions

- take first dose 1/2 to 1 hour before starting activity
- dults and children 12 years and over: 1 to 2 tablets once daily, or as directed by a doctor

Other information

store at room temperature 20°-25°C (68°-77°F)

Inactive ingredients

corn starch, colloidal silicon dioxide, D&C yellow no. 10 aluminum lake, lactose, magnesium stearate, microcrystalline cellulose

Questions?

Questions?1-800-382-7219 Dramamine.com

Dramamnie® Less Drowsy, Lil' Drug Store®

#1

Pharmacist

Recommended

BRAND

MECLIZINE HYDROCHLORIDE

TABLETS /ANTIEMETIC

Dramamine®

notion sickness

LESS DROWSY

Dual Action:

Prevents & Relieves Nausea,

Dizziness and Vomiting

UP TO

24

HOURS

2 Tablets

(25 MG EACH)

[Lil' Drug Store logo]